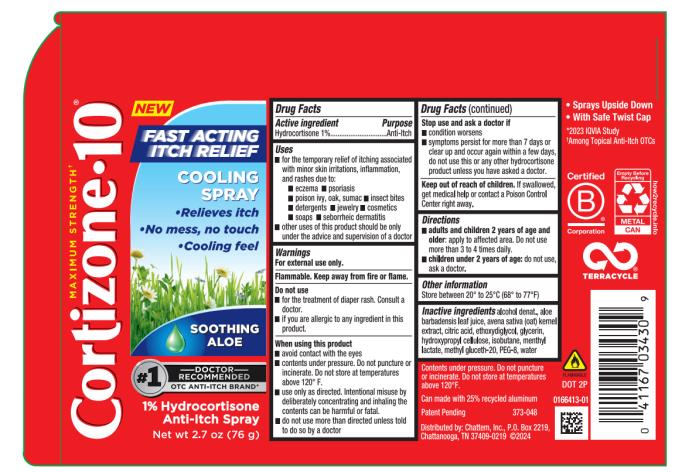 DRUG LABEL: Cortizone 10 Fast Acting Itch Relief Cooling
NDC: 41167-0343 | Form: SPRAY
Manufacturer: Chattem, Inc.
Category: otc | Type: HUMAN OTC DRUG LABEL
Date: 20250103

ACTIVE INGREDIENTS: HYDROCORTISONE 1 g/100 g
INACTIVE INGREDIENTS: ALCOHOL; ALOE VERA LEAF; OAT; CITRIC ACID MONOHYDRATE; DIETHYLENE GLYCOL MONOETHYL ETHER; GLYCERIN; HYDROXYPROPYL CELLULOSE, UNSPECIFIED; ISOBUTANE; MENTHYL LACTATE, (-)-; METHYL GLUCETH-20; POLYETHYLENE GLYCOL 400; WATER

Cortizone 10 Cooling Spray

Drug Facts

Active ingredients

Hydrocortisone 1%

Purpose

Anti-Itch

Uses

■ for the temporary relief of itching associated with minor skin irritations, inflammation, and rashes due to:

■ eczema ■ psoriasis ■ poison ivy, oak, sumac ■ insect bites ■ detergents ■ jewelry ■ cosmetics

■ soaps ■ seborrheic dermatitis

■ other uses of this product should be only under the advice and supervision of a doctor

Warnings

For external use only.

Flammable. Keep away from fire or flame.

Do not use

■ for the treatment of diaper rash. Consult a doctor.

■ if you are allergic to any ingredient in this product.

When using this product

■ avoid contact with the eyes

■ contents under pressure. Do not puncture or incinerate. Do not store at temperatures above 120° F.

■ use only as directed. Intentional misuse by deliberately concentrating and inhaling the contents can be harmful or fatal.

■ do not use more than directed unless told to do so by a doctor

Stop use and ask a doctor if

■ condition worsens

■ symptoms persist for more than 7 days or clear up and occur again within a few days, do not use this or any other hydrocortisone product unless you have asked a doctor.

Keep out of reach of children.

If swallowed, get medical help or contact a Poison Control Center right away.

Directions

■ adults and children 2 years of age and older: apply to affected area. Do not use more than 3 to 4 times daily.

■ children under 2 years of age: do not use, ask a doctor.

Other information

Store between 20° to 25°C (68° to 77°F)

Inactive ingredients

alcohol denat., aloe barbadensis leaf juice, avena sativa (oat) kernel extract, citric acid, ethoxydiglycol, glycerin, hydroxypropyl cellulose, isobutane, menthyl lactate, methyl gluceth-20, PEG-8, water

Principal Display Panel

Cortizone 10
FAST ACTING
ITCH RELIEF
COOLING SPRAY
SOOTHING ALOE
1% Hydrocortisone
Anti-Itch Spray
Net wt 2.7 oz (76 g)